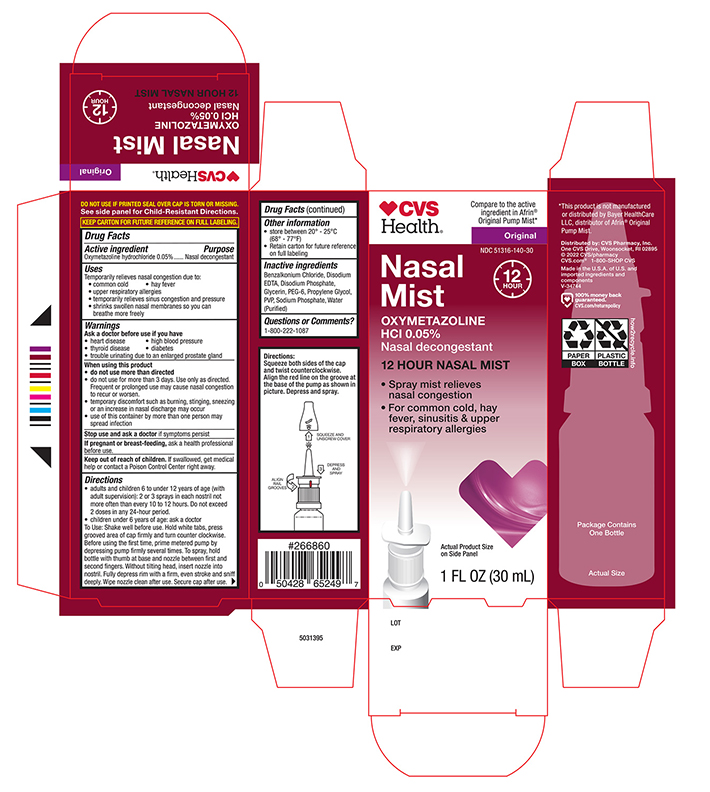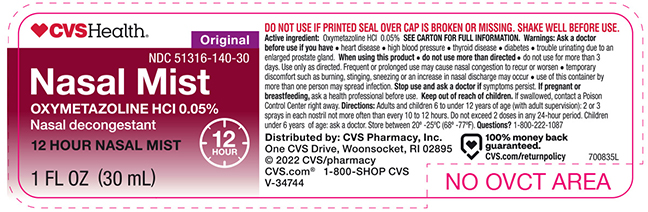 DRUG LABEL: CVS Original Nasal Mist
NDC: 51316-140 | Form: SPRAY
Manufacturer: CVS PHARMACY, INC
Category: otc | Type: HUMAN OTC DRUG LABEL
Date: 20241112

ACTIVE INGREDIENTS: OXYMETAZOLINE HYDROCHLORIDE 0.05 g/100 mL
INACTIVE INGREDIENTS: POLYETHYLENE GLYCOL 300; GLYCERIN; PROPYLENE GLYCOL; EDETATE DISODIUM; SODIUM PHOSPHATE, MONOBASIC; SODIUM PHOSPHATE, DIBASIC, ANHYDROUS; POVIDONE; BENZALKONIUM CHLORIDE; WATER

Active Ingredient

Oxymetazoline Hydrochloride 0.05%

Purpose

Nasal Decongestant

Uses

Temporarily relieves nasal congestion due to:

- common cold
- hay fever
- sinusitis
- upper respiratory allergies
- shrinks swollen membranes so you can breathe more freely

Ask a Doctor before use if you have

- heart diease
- high blood pressure
- diabetes
- thyroid disease
- trouble urinating due to enlarged prostate gland

When using this product

- Do not use more than directed
- do not use for more than three days, Use only as directed. Frequent or prolonged use may cause nasal congestion to recur or worsen.
- temporary discomfort such as burning, stinging, sneezing or an increase in nasal discharge may occur.
- use of this container by more than one person may spread infection.

stop use and ask a doctor if

symptoms persist.

PREGNANCY OR BREAST FEEDING

ask a health professional before use.

Keep out of the reach of children

if swallowed, get medical help or contact a Poison Control Center right away.

Directions

- Adults and children 6 to under 12 years of age (with adult supervision):2 or 3 sprays in each nostril not more than every 10 to 12 hours. Do not exceed 2 doses in any 24-hour period.
- Children under 6 years of age consult a doctor.To spray, squeeze bottle quickly and firmly. Do not tilt head backwards while spraying, wipe nozzle clean after use.

Other information

store between 20° and 25°C (68° to 77°F)
retain carton for future reference on full labeling

Inactive Ingredients:

benzalkonium chloride, edetate disodium, glycerin, polyethylene glycol, povidone, propylene glycol, sodium phosphate dibasic, sodium phosphate monobasic, water

Principal Display panel - Bottle label

CVS Original Nasal Spray NDC 51316-140-30

Oxymetazoline Hydrochloride 0.05%

12 hour Nasal Mist

Nasal Decongestant

NET WT 1.0 FLOZ (30ml)

Principal Display panel - Carton label

CVS Original Nasal Spray NDC 51316-140-30
Oxymetazoline Hydrochloride 0.05%

12 hour Nasal Mist

Nasal Decongestant

NET WT 1.0 FLOZ (30ml)